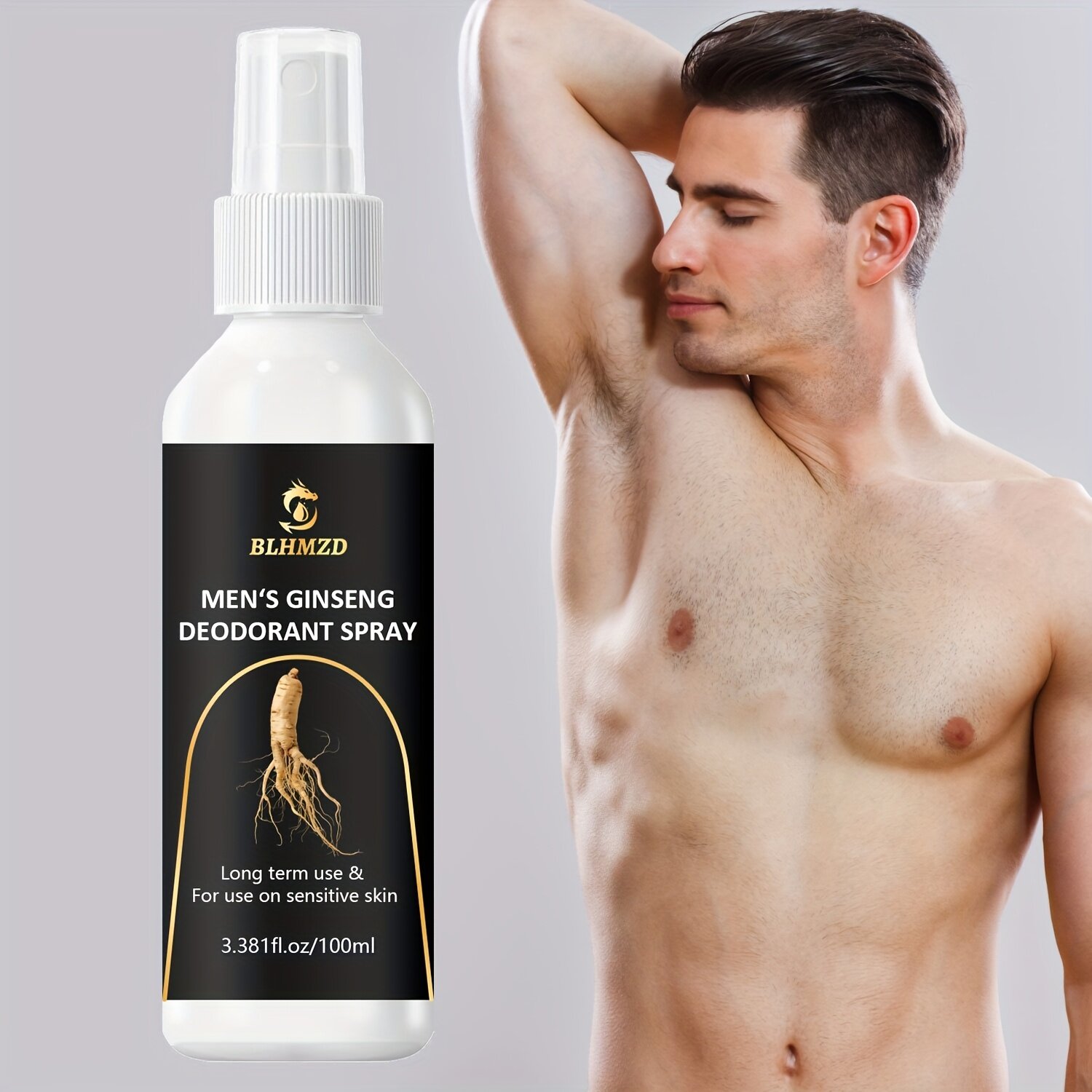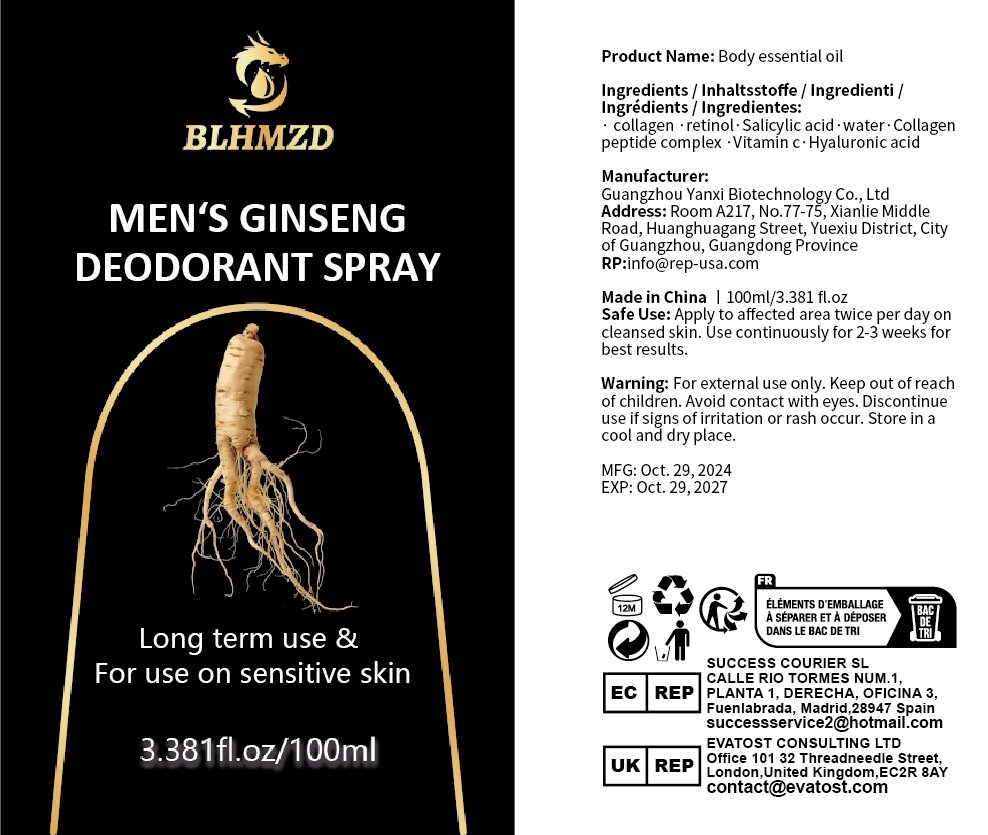 DRUG LABEL: Body essential oil
NDC: 84025-315 | Form: OIL
Manufacturer: Guangzhou Yanxi Biotechnology Co., Ltd
Category: otc | Type: HUMAN OTC DRUG LABEL
Date: 20250107

ACTIVE INGREDIENTS: RETINOL 5 mg/100 mL; HYALURONIC ACID 3 mg/100 mL
INACTIVE INGREDIENTS: WATER

DOSAGE AND ADMINISTRATION

Apply to affected area twice per day oncleansed skin.Use continuously for 2-3 weeks forbest results.

WARNINGS

keep out of children

INACTIVE INGREDIENT

Aqua

INDICATIONS AND USAGE

for body care

keep out of children

PURPOSE

Eliminate armpit odor